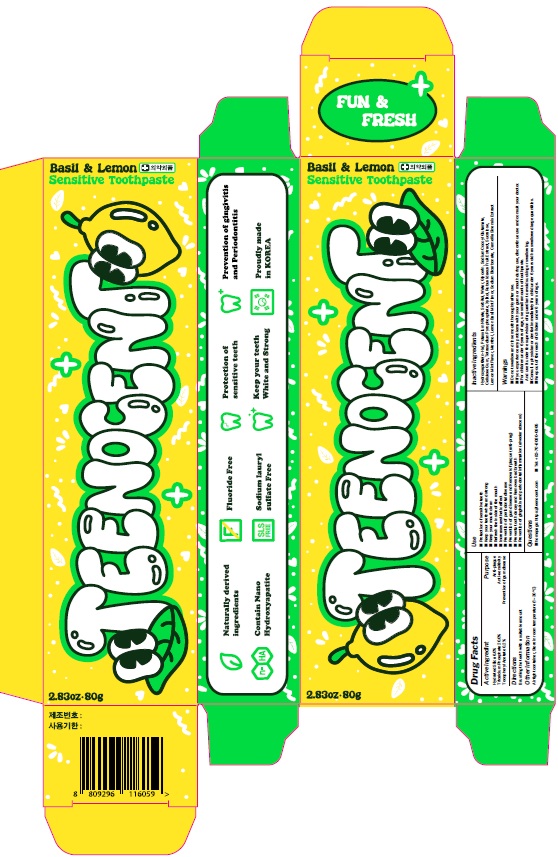 DRUG LABEL: TEENOCENT SENSITIVE TOOTH
NDC: 84176-010 | Form: PASTE, DENTIFRICE
Manufacturer: FROMANGEL
Category: otc | Type: HUMAN OTC DRUG LABEL
Date: 20240609

ACTIVE INGREDIENTS: HYDRATED SILICA 6 g/100 g
INACTIVE INGREDIENTS: TRICALCIUM PHOSPHATE; WATER; .ALPHA.-TOCOPHEROL ACETATE; GLYCERIN; SORBITOL

ACTIVE INGREDIENT

Hydrated Silica 6.0%

Tricalcium Phosphate 20.0%

Tocopheryl Acetate 0.2%

INACTIVE INGREDIENT

Sorbitol, Water, Glycerin, Sodium Cocoyl Glutamate, Cellulose Gum, Tetrasodium Pyrophosphate, Potassium Nitrate, Hydroxyapatite, Xylitol, Rubus Idaeus Fruit Extract, Lemon Mint Flavor, Menthol, Lemon Basil Mint Flavor, Sodium Bicarbonate, Sucralose, Camellia Sinensis Extract

PURPOSE

Anti-plaque, Prevention of gum disease

WARNINGS

■ Do not swallow and rinse mouth thoroughly after use.

■ If you experience any problems with your gums or mouth during use,

discontinue use and consult your doctor.

■ For children under 6 years of age, use small amounts of toothpaste.

And use it under the supervision of a guardian to avoid sucking or swallowing.

■ Consult a physician or dentist immediately if a child under 6 years old has

swallowed large quantities.

■ Keep out of the reach of children under 6 years of age.

KEEP OUT OF REACH OF CHILDREN

■ Keep out of the reach of children under 6 years of age.

INDICATIONS AND USAGE

Use(s)

■ Keep your teeth white and strong

■ Keep your mouth clean

■ Refresh the inside of the mouth

■ Prevents tooth decay and Removes bad breath

■ Increases aesthetic effect

■ Prevention of gingivitis and periodontal inflammation (alveolar abscess)

■ Prevention of periodontal disease

■ Prevention of gum disease and Removal of plaque (anti-prag)

■ Protection of sensitive teeth

Directions

■ Brushing the teeth with a suitable amount

OTHER SAFETY INFORMATION

■ Airtight container, Store in room temperature (1~30℃)

QUESTIONS

■ homepage: https://teenocent.com/

■ Tel: +82-70-8080-0965